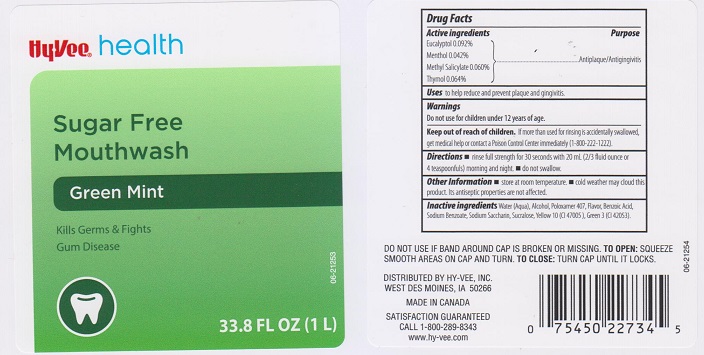 DRUG LABEL: HYVEE HEALTH GREEN MINT SUGAR FREE
NDC: 42507-562 | Form: MOUTHWASH
Manufacturer: HYVEE INC
Category: otc | Type: HUMAN OTC DRUG LABEL
Date: 20160309

ACTIVE INGREDIENTS: EUCALYPTOL 0.92 mg/1 mL; MENTHOL 0.42 mg/1 mL; METHYL SALICYLATE 0.60 1/1 mL; THYMOL 0.64 1/1 mL
INACTIVE INGREDIENTS: WATER; ALCOHOL; POLOXAMER 407; BENZOIC ACID; SODIUM BENZOATE; SACCHARIN SODIUM; SUCRALOSE; FD&C GREEN NO. 3; D&C YELLOW NO. 10

DRUG FACTS

Active ingredients

Eucalyptol 0.092%, Menthol 0.042%, Methyl Salicylate 0.060%, Thymol 0.064%

Purpose

Antiplaque/Antigingivitis

Uses

to help reduce and prevent plaque and gingivitis.

Warnings

Do not use for children under 12 years of age.

Keep out of reach of children.

If more than used for rinsing is accidentally swallowed, get medical help or contact a Poison Control Center immediately (1-800-222-1222).

Directions

- rinse full strength for 30 seconds with 20 mL (2/3 fluid ounce or 4 teaspoonfuls) morning and night.
- do not swallow.

Other information

- store at room temperature.
- cold weather may cloud this product. Its antiseptic properties are not affected.

Inactive ingredients

Water (Aqua), Alcohol, Poloxamer 407, Flavor, Benzoic Acid, Sodium Benzoate, Sodium Saccharin, Sucralose, Yellow 10 (CI 47005), Green 3 (CI 42053).